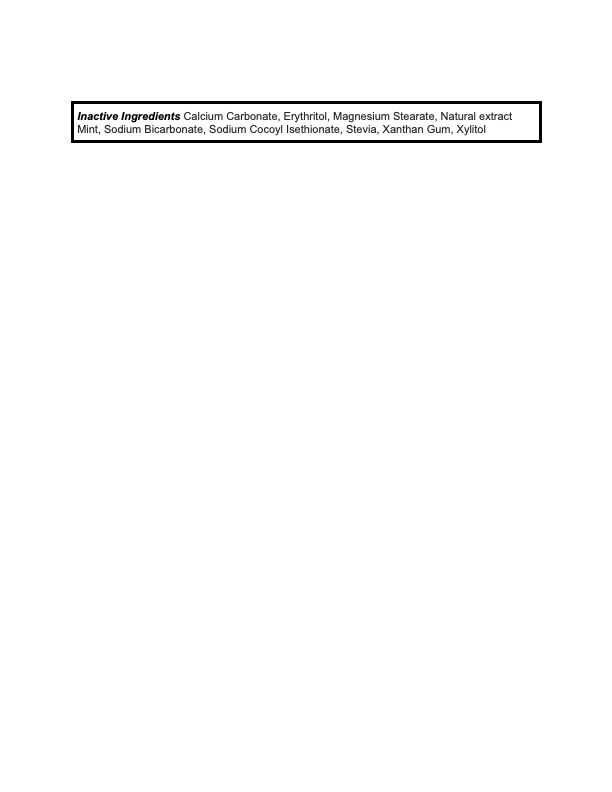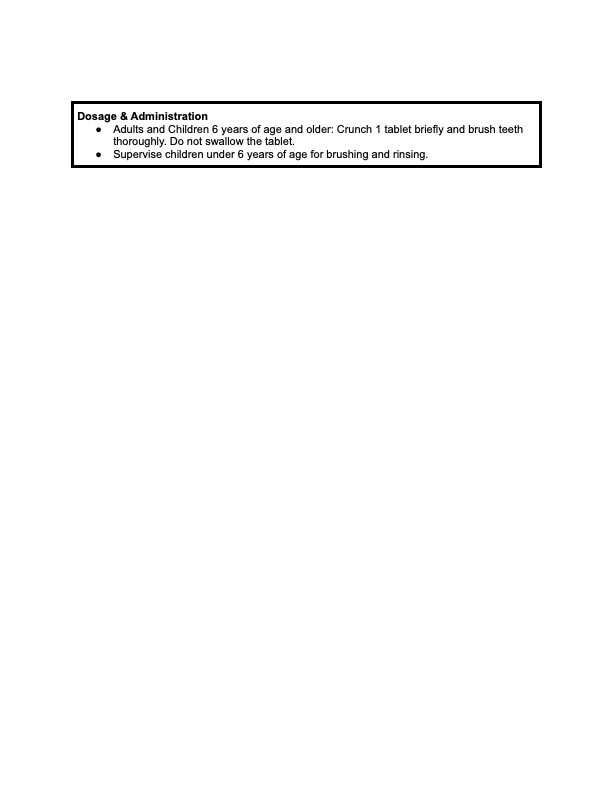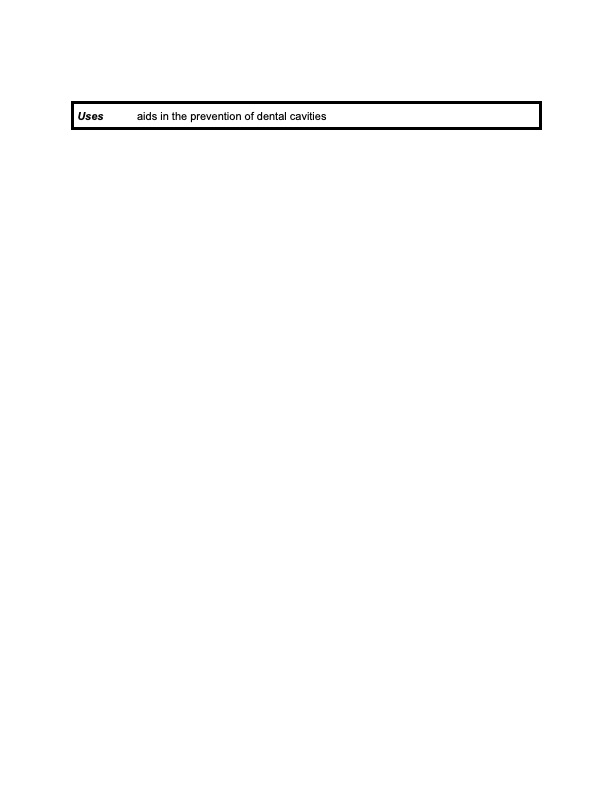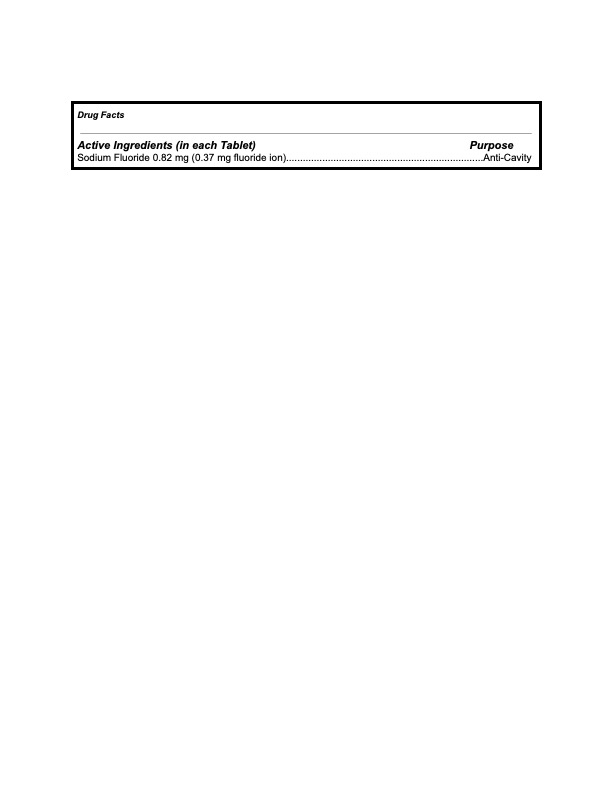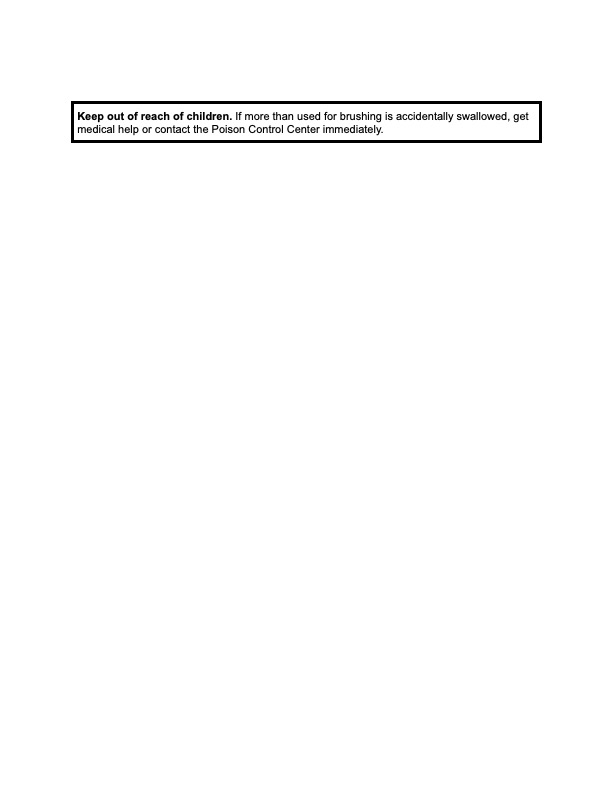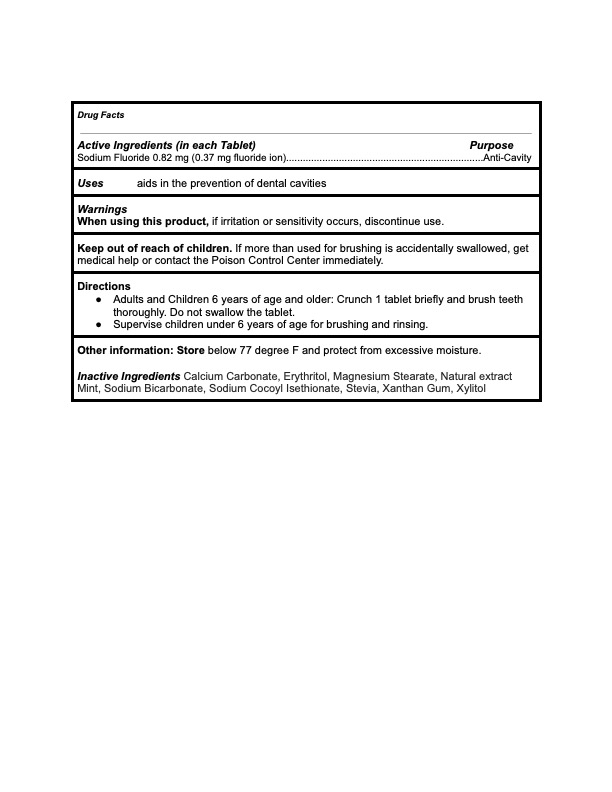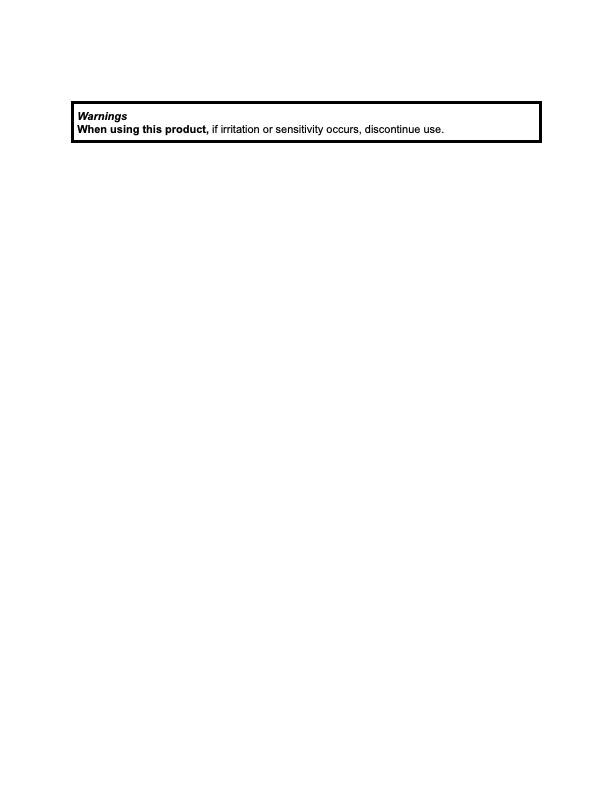 DRUG LABEL: KAYLAAN
NDC: 82091-114 | Form: TABLET, CHEWABLE
Manufacturer: Kaylaan LLC
Category: otc | Type: HUMAN OTC DRUG LABEL
Date: 20230112

ACTIVE INGREDIENTS: SODIUM FLUORIDE 0.37 mg/440 mg
INACTIVE INGREDIENTS: STEVIA LEAF; CALCIUM CARBONATE; BLUEBERRY; ERYTHRITOL; XYLITOL; MAGNESIUM STEARATE; SODIUM BICARBONATE; SODIUM COCOYL ISETHIONATE; XANTHAN GUM

Kaylaan Blueberry Toothpaste Tablet Refill